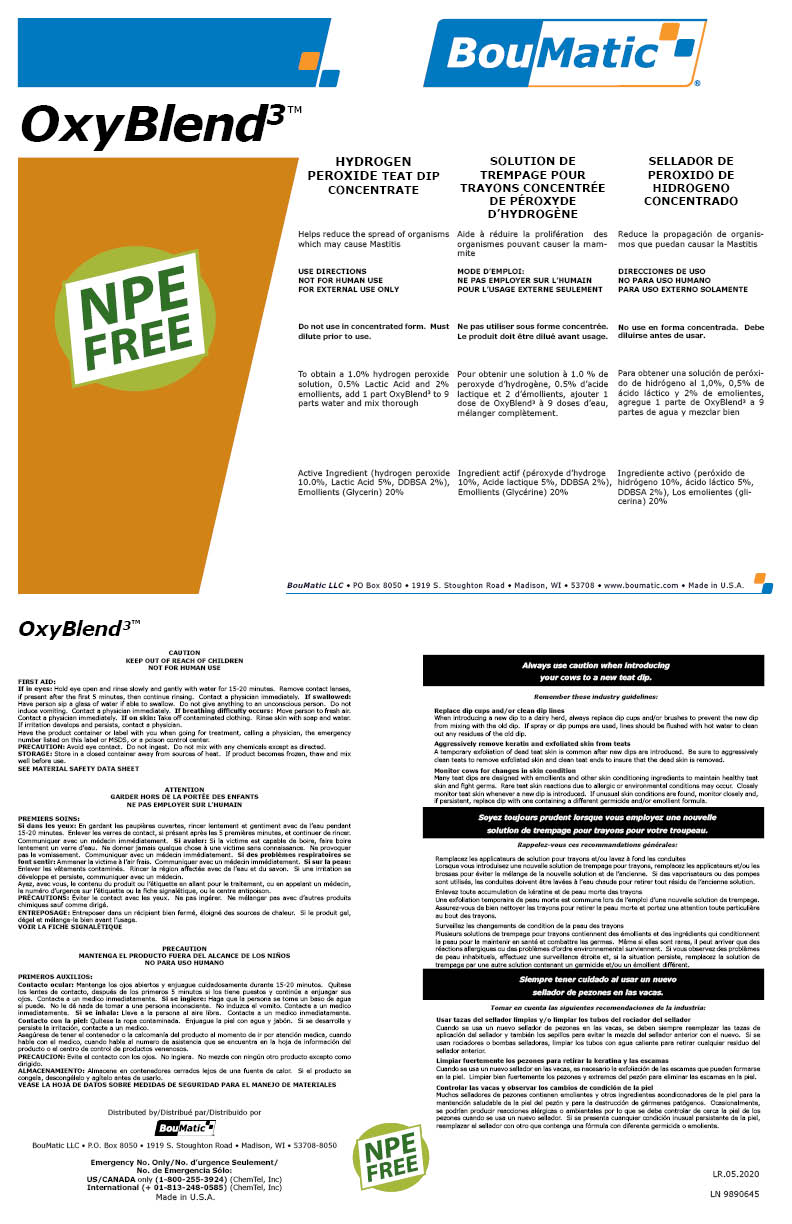 DRUG LABEL: OxyBlend3
NDC: 48106-2050 | Form: LIQUID
Manufacturer: BOUMATIC, LLC
Category: animal | Type: OTC ANIMAL DRUG LABEL
Date: 20230310

ACTIVE INGREDIENTS: HYDROGEN PEROXIDE 10 g/100 g; LACTIC ACID 5 1/100 g
INACTIVE INGREDIENTS: WATER; GLYCERIN; ANHYDROUS CITRIC ACID; UREA; SODIUM HYDROXIDE

OxyBlend3

Claim of effectiveness.

Helps reduce the spread of organisms
which may cause Mastitis

Use Directions

NOT FOR HUMAN USE
FOR EXTERNAL USE ONLY
Do not use in concentrated form. Must
dilute prior to use.

First Aid

If in eyes: Hold eye open and rinse slowly and gently with water for 15-20 minutes. Remove contact lenses,
if present after the first 5 minutes, then continue rinsing. Contact a physician immediately. If swallowed:
Have person sip a glass of water if able to swallow. Do not give anything to an unconscious person. Do not
induce vomiting. Contact a physician immediately. If breathing difficulty occurs: Move person to fresh air.
Contact a physician immediately. If on skin: Take off contaminated clothing. Rinse skin with soap and water.
If irritation develops and persists, contact a physician.
Have the product container or label with you when going for treatment, calling a physician, the emergency
number listed on this label or MSDS, or a poison control center.

Precautions & Hazards

PRECAUTION: Avoid eye contact. Do not ingest. Do not mix with any chemicals except as directed.

General Storage

STORAGE: Store in a closed container away from sources of heat. If product becomes frozen, thaw and mix
well before use.